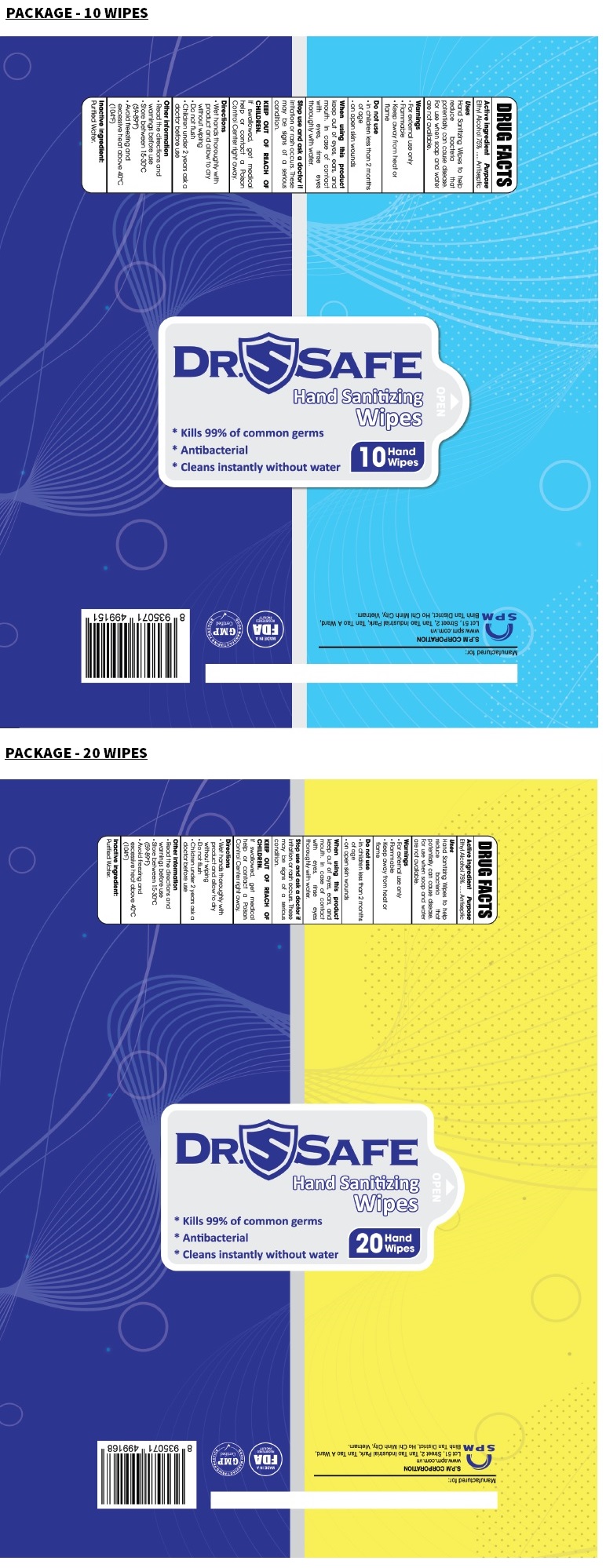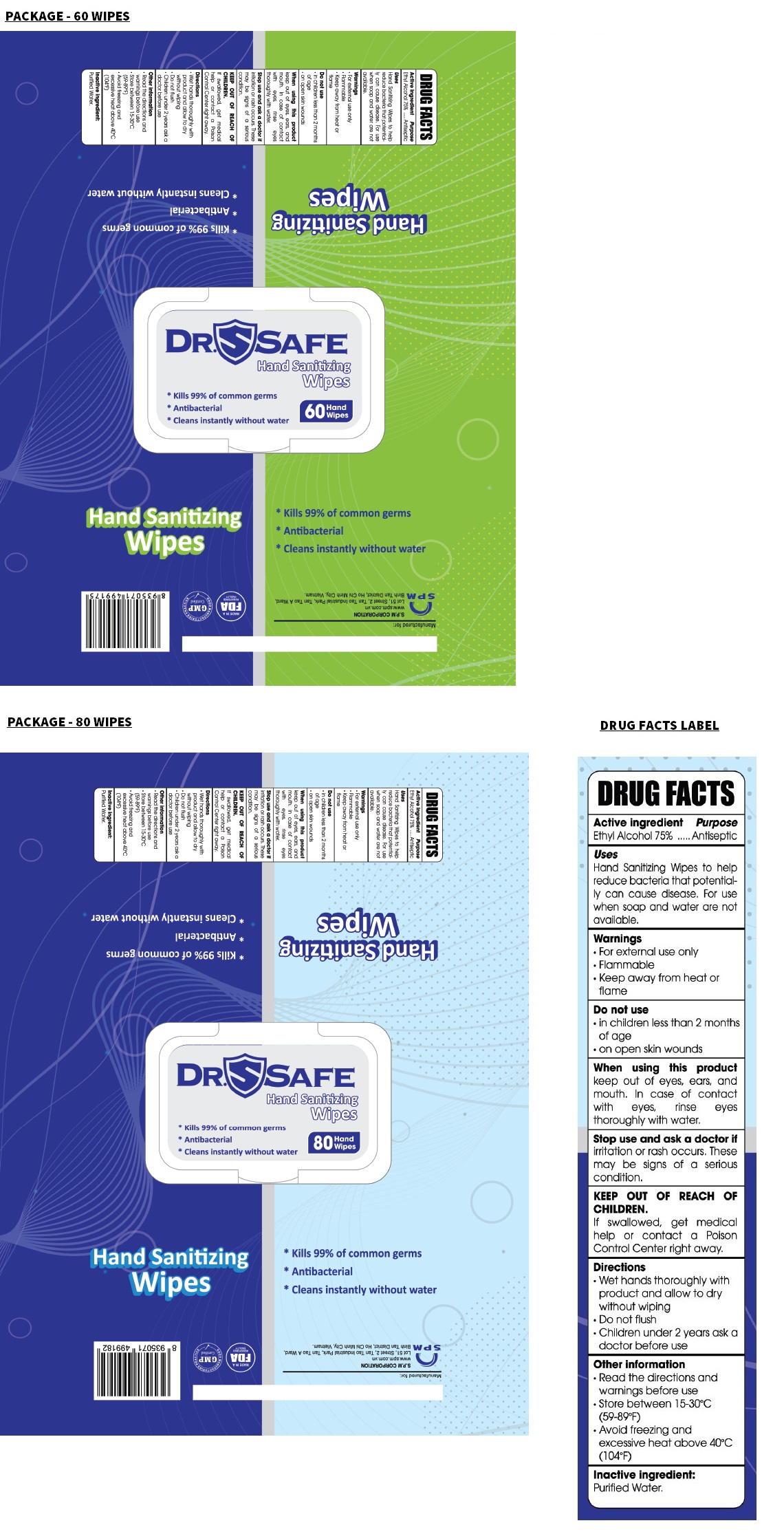 DRUG LABEL: DR SAFE HAND SANITIZING WIPES
NDC: 78898-775 | Form: CLOTH
Manufacturer: Eco Wipes Vietnam Corporation
Category: otc | Type: HUMAN OTC DRUG LABEL
Date: 20210211

ACTIVE INGREDIENTS: ALCOHOL 75 mL/100 mL
INACTIVE INGREDIENTS: WATER

DR. SAFE Hand Sanitizing Wipes

Active ingredient

Ethyl Alcohol 75%

Purpose

Antiseptic

Uses

Hand Sanitizing Wipes to help reduce bacteria that potentially can cause disease. For use when soap and water are not available.

Warnings

• For external use only

• Flammable

• Keep away from heat or flame

Do not use

• in children less than 2 months of age

• on open skin wounds

When using this product

keep out of eyes, ears, and mouth. In case of contact with eyes, rinse eyes thoroughly with water.

Stop use and ask a doctor if

irritation or rash occurs. These may be signs of a serious condition.

KEEP OUT OF REACH OF CHILDREN.

If swallowed, get medical help or contact a Poison Control Center right away.

Directions

• Wet hands thoroughly with product and allow to dry without wiping

• Do not flush

• Children under 2 years ask a doctor before use

Other information

• Read the directions and warnings before use

• Store between 15-30°C (59-89°F)

• Avoid freezing and excessive heat above 40°C (104°F)

Inactive ingredient:

Purified Water.

* Kills 99% of common germs

* Antibacterial

* Cleans instantly without water

Manufactured for:

S.P.M CORPORATION

www.spm.com.vn

Lot 51, Street 2, Tan Tao Industrial Park, Tan Tao A Ward,

Binh Tan District, Ho Chi Minh City, Vietnam.